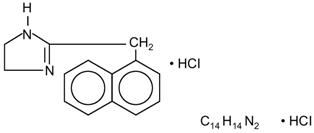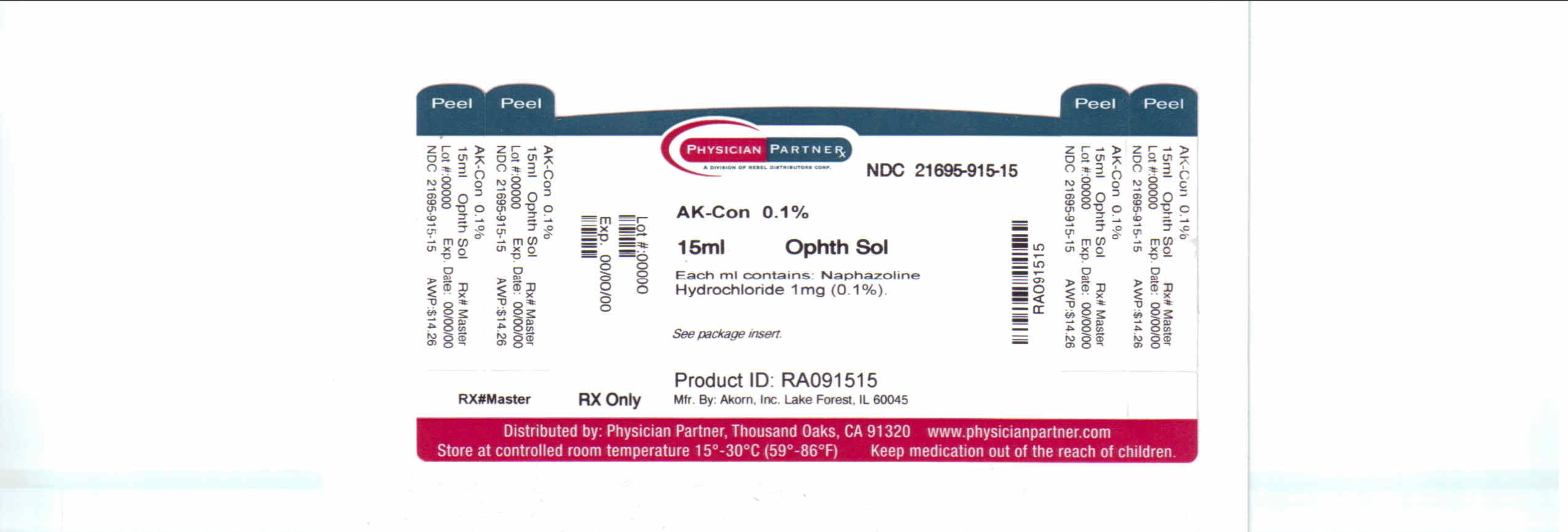 DRUG LABEL: AK-Con
NDC: 21695-915 | Form: SOLUTION
Manufacturer: Rebel Distributors Corp.
Category: prescription | Type: HUMAN PRESCRIPTION DRUG LABEL
Date: 20110330

ACTIVE INGREDIENTS: naphazoline hydrochloride 1 mg/1 mL
INACTIVE INGREDIENTS: edetate disodium; water; sodium chloride; SODIUM CARBONATE; BENZALKONIUM CHLORIDE; HYDROCHLORIC ACID; BORIC ACID

ALBALON®
(naphazoline hydrochloride ophthalmic solution, USP) 0.1%

Sterile

DESCRIPTION

Naphazoline hydrochloride, an ocular vasoconstrictor, is an imidazoline derivative sympathomimetic amine. It occurs as a white, odorless crystalline powder having a bitter taste and is freely soluble in water and in alcohol. The active ingredient is represented by the structural formula:

Chemical Name:

2-(1-Naphthylmethyl)-2-imidazoline monohydrochloride

Contains:

Active: naphazoline HCl 1 mg (0.1%). Preservative: benzalkonium chloride 0.1mg (0.01%).
Inactives: Boric acid; edetate disodium; purified water; sodium chloride; sodium carbonate; and hydrochloric acid may be added to adjust the pH (5.5 to 7.0).

CLINICAL PHARMACOLOGY

Naphazoline constricts the vascular system of the conjunctiva. It is presumed that this effect is due to direct stimulation of the drug upon the alpha-adrenergic receptors in the arterioles of the conjunctiva, resulting in decreased conjunctival congestion. Naphazoline belongs to the imidazoline class of sympathomimetics.

INDICATIONS AND USAGE

Naphazoline Hydrochloride Ophthalmic Solution is indicated for use as a topical ocular vasoconstrictor.

CONTRAINDICATIONS

Contraindicated in the presence of an anatomically narrow angle or in narrow-angle glaucoma or in persons who have shown hypersensitivity to any component of this preparation.

WARNINGS

Patients under therapy with MAO inhibitors may experience a severe hypertensive crisis if given a sympathomimetic drug. Use in children, especially infants, may result in CNS depression leading to coma and marked reduction in body temperature.

PRECAUTIONS

General:

For topical ophthalmic use only. Use with caution in the presence of hypertension, cardiovascular abnormalities, hyperglycemia (diabetes), hyperthyroidism, infection or injury.

Patient Information:

Patients should be advised to discontinue the drug and consult a physician if relief is not obtained within 48 hours of therapy, if irritation, blurring or redness persists or increases, or if symptoms of systemic absorption occur, i.e., dizziness, headache, nausea, decrease in body temperature, or drowsiness.

To prevent contaminating the dropper tip and solution, do not touch the eyelids or the surrounding area with the dropper tip of the bottle. If solution changes color or becomes cloudy, do not use.

Drug Interactions:

Concurrent use of maprotiline or tricyclic antidepressants and naphazoline may potentiate the pressor effect of naphazoline. Patients under therapy with MAO inhibitors may experience a severe hypertensive crisis if given a sympathomimetic drug. (See WARNINGS.)

Pregnancy:

Pregnancy Category C: Animal reproduction studies have not been
conducted with naphazoline. It is also not known whether naphazoline can cause fetal harm when administered to a pregnant woman or can affect reproduction capacity. Naphazoline should be given to a pregnant woman only if clearly needed.

Nursing Mothers:

It is not known whether naphazoline is excreted in human milk. Because many drugs are excreted in human milk, caution should be exercised when naphazoline is administered to a nursing woman.

Pediatric Use:

Safety and effectiveness in pediatric patients have not been established. See “WARNINGS.” and “CONTRAINDICATIONS.”

ADVERSE REACTIONS

Ocular: Mydriasis, increased redness, irritation, discomfort, blurring, punctate keratitis, lacrimation, increased intraocular pressure.

Systemic: Dizziness, headache, nausea, sweating , nervousness, drowsiness, weakness, hypertension, cardiac irregularities, and hyperglycemia.

DOSAGE AND ADMINISTRATION

Instill one or two drops in the conjunctival sac(s) every three to four hours as needed.

HOW SUPPLIED

Naphazoline Hydrochloride Ophthalmic Solution, USP) is supplied as a sterile 0.1% solution in

15 mL plastic dropper bottles. NDC 17478-216-12

Storage: Store at 20° to 25°C (68° to 77°F). Keep container tightly closed.

Rx Only

Manufactured by:

Akorn Inc.
Lake Forest, IL 60045

Repackaged by:

Rebel Distributors Corp

Thousand Oaks, CA 91320